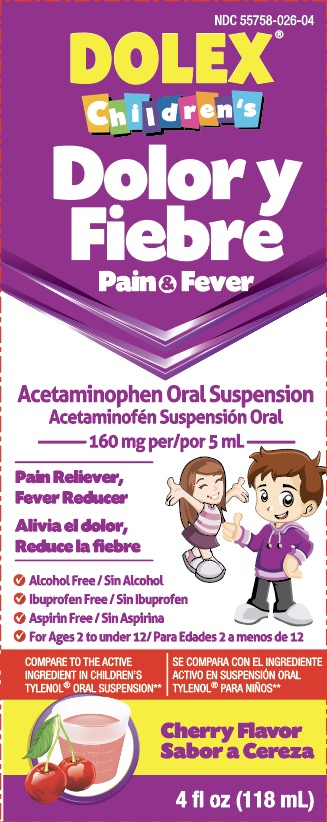 DRUG LABEL: Dolex
NDC: 55758-026 | Form: SUSPENSION
Manufacturer: Pharmadel LLC
Category: otc | Type: HUMAN OTC DRUG LABEL
Date: 20240304

ACTIVE INGREDIENTS: ACETAMINOPHEN 160 mg/5 mL
INACTIVE INGREDIENTS: XANTHAN GUM; CELLULOSE, MICROCRYSTALLINE; GLYCERIN; BUTYLPARABEN; ANHYDROUS CITRIC ACID; FD&C RED NO. 40; HIGH FRUCTOSE CORN SYRUP; PROPYLENE GLYCOL; WATER; SODIUM BENZOATE; SORBITOL; SUCRALOSE; CARBOXYMETHYLCELLULOSE SODIUM, UNSPECIFIED FORM

Dolex Children Pain & Fever (APTA)

Active ingredient & Purpose

Active ingredient (in each 5 mL) | Purpose
Acetaminophen 160 mg | Pain reliever/ fever reducer

Uses

For the temporary relief of minor aches and pain due to:

- a cold
- headache
- sore throat
- toothache
- and to reduce fever

Warnings

Liver warning: This product contains acetaminophen. Severe liver damage may occur if your child takes:

- more than 5 doses in 24 hours, which is the maximum daily amount
- with other drugs containing acetaminophen

Sore throat warning: If sore throat is severe, persists for more than 2 days, is accompanied or followed by fever, headache, rash, nausea, or vomiting, consult a doctor promptly.

Do not use

- with any other drug containing acetaminophen (prescription or nonprescription). If you are not sure whether a drug contains acetaminophen, ask a doctor or pharmacist.
- If your child is allergic to acetaminophen or any other of the inactive ingredients in this product

Ask a doctor before use if your child has

liver disease.

Ask a doctor or pharmacist before use if your child is

taking the blood thinning drug warfarin.

When using this product

do not exceed recommended dose (see overdose warning).

Stop use and ask a doctor if

- pain gets worse or lasts more than 5 days
- fever gets worse or lasts more than 3 days
- any new symptoms occur
- redness or swelling is present

Keep out of reach of children.

Overdose warning:

Taking more than the recommended dose (overdose) may cause liver damage. In case of overdose, get medical help or contact a Poison Control Center right away at 1-800-222-1222. Prompt medical attention is critical for adults as well as for children even if you do not notice any signs or symptoms.

Directions

- this product does not contain directions or complete warnings for adult use

- shake well before using
- use only enclosed dosing cup. Do not use any other dosing device

- mL = milliliter

- use the dose that corresponds to your child's age

Age (years) | Dose (mL)*
under 2 | consult a doctor
2 to under 4 | 5 mL
4 to under 5 | 7.5 mL
6 to under 8 | 10 mL
9 to under 10 | 12.5 mL
11 to under 12 | 15 mL

*Dose may be repeated every 4 hours while symptoms persist, up to five times a day or as directed by a doctor.

Other information

- each 5 mL contains: sodium 3 mg
- store between 68-77° F (20-25° C)
- do not refrigerate
- keep carton for full directions for use

Inactive ingredients

anhydrous citric acid, butylparaben, FD&C red # 40, flavor, glycerin, high fructose corn syrup, microcrystalline cellulose and carboxymethylcellulose sodium, propylene glycol, purified water, sodium benzoate, sorbitol solution, sucralose, xanthan gum

Questions?

+1-866-359-3478 (9 AM - 5 PM EST) or pharmadel.com

** This product is not manufactured or distributed by Mcneil Consumer Healthcare, distributor of Children’s Tylenol® Oral Suspension.

Distributed by:

PHARMADEL LLC.

New Castle, DE 19720